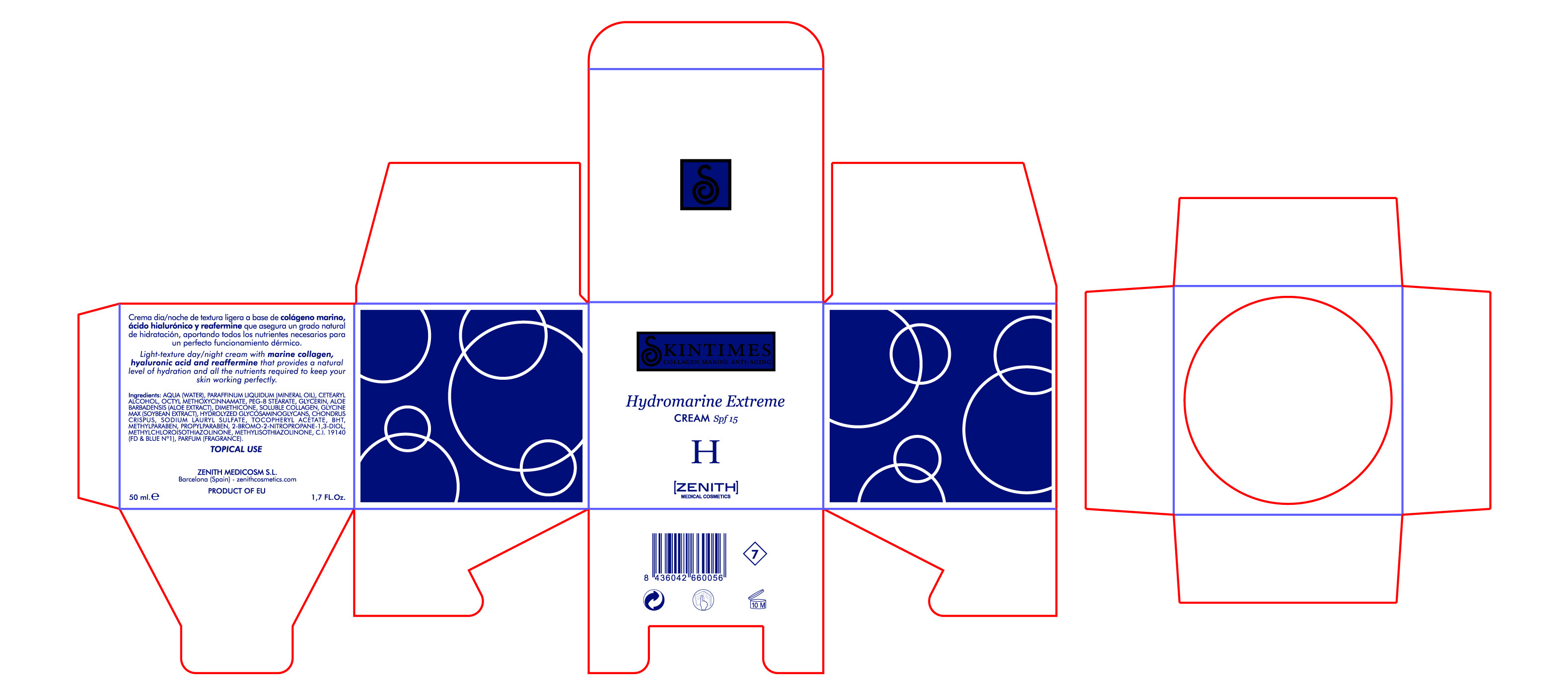 DRUG LABEL: Hydromarine
NDC: 42248-101 | Form: CREAM
Manufacturer: Zenith Medicosm SL
Category: otc | Type: HUMAN OTC DRUG LABEL
Date: 20120121

ACTIVE INGREDIENTS: OCTINOXATE 3.75 mL/50 mL
INACTIVE INGREDIENTS: ALOE; PROPYLPARABEN; ALPHA-TOCOPHEROL ACETATE; GLYCERIN; TRICHLOROETHANE; SODIUM LAURYL SULFATE; WATER; MINERAL OIL; CETOSTEARYL ALCOHOL; PEG-8 STEARATE; DIMETHICONE; SOYBEAN; CHONDRUS CRISPUS; BUTYLATED HYDROXYTOLUENE; PROPYLPARABEN; BRONOPOL; HYDROLYZED GLYCOSAMINOGLYCANS (BOVINE; 50000 MW); METHYLCHLOROISOTHIAZOLINONE; METHYLPARABEN; COLLAGEN, SOLUBLE, FISH SKIN; FD&C BLUE NO. 1

Drug Facts

Active Ingredient

Octinoxate 7.5%

Description

Light-texture day/night cream with marine collagen, hyaluronic acid and reaffermine that provides a natural level of hydration and all the nutrients required to keep your skin working perfectly.

50ml. 1.7 fl. Oz

Warning

TOPICAL USE